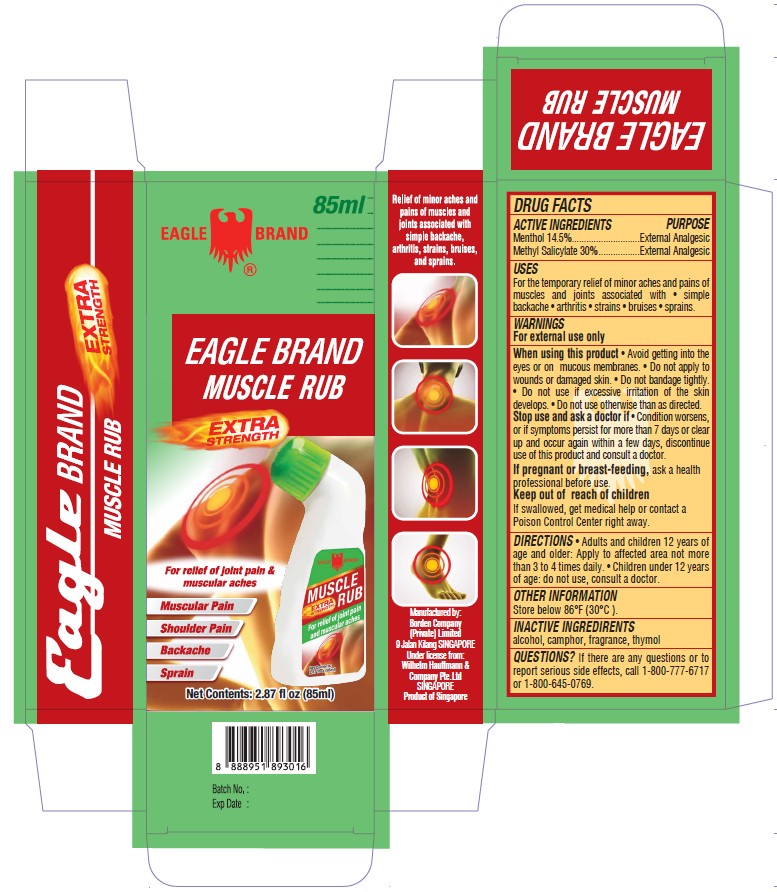 DRUG LABEL: Eagle Brand
NDC: 43405-011 | Form: LIQUID
Manufacturer: Borden Company (Private) Limited
Category: otc | Type: HUMAN OTC DRUG LABEL
Date: 20250715

ACTIVE INGREDIENTS: MENTHOL 14.5 g/100 mL; METHYL SALICYLATE 30 g/100 mL
INACTIVE INGREDIENTS: CAMPHOR (SYNTHETIC); THYMOL; ALCOHOL

Eagle Brand Muscle Rub

Active Ingredients

- Menthol 14.5%
- Methyl Salicylate 30%

Purpose

External Analgesic

Uses

For temporary relief of minor aches and pains of muscles and joints associated with ■ simple backache ■ arthritis ■ strains ■ bruises ■ sprains.

Warnings

For external use only

When using this product

- Avoid getting into the eyes or mucous membranes.
- Do not apply to wounds or damaged skin.
- Do not bandage tightly.
- Do not use otherwise than as directed.

Stop use and ask doctor if

Condition worsens, or if symptoms persist for more than 7 days or clear up and occur again within a few days, discontinue use of this product and consult a doctor.

If pregnant or breast-feeding

Ask a health professional before use.

Keep out of reach of children

If swallowed, get medical help medical help or contact a Poison Control Centre right away.

Directions

■ adults and children 12 years of age and older: apply to affected area not more than 3 to 4 times daily.

■ children under 12 years of age: do not use, consult a doctor.

Other information

Store below 86oF (30oC).

Inactive ingredients

alcohol, camphor, fragrance, thymol

Questions?

If there are any questions or to report serious side effects, call 1-800-777-6717 or 1-800-645-0769.

Package Label

85ml NDC: 43405-011-85